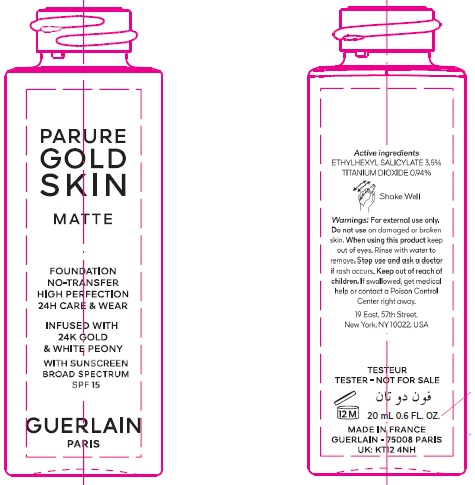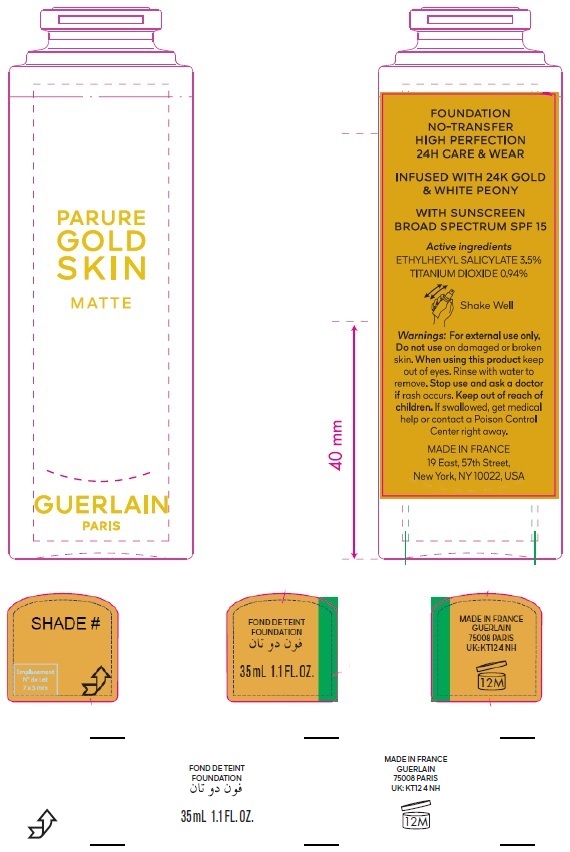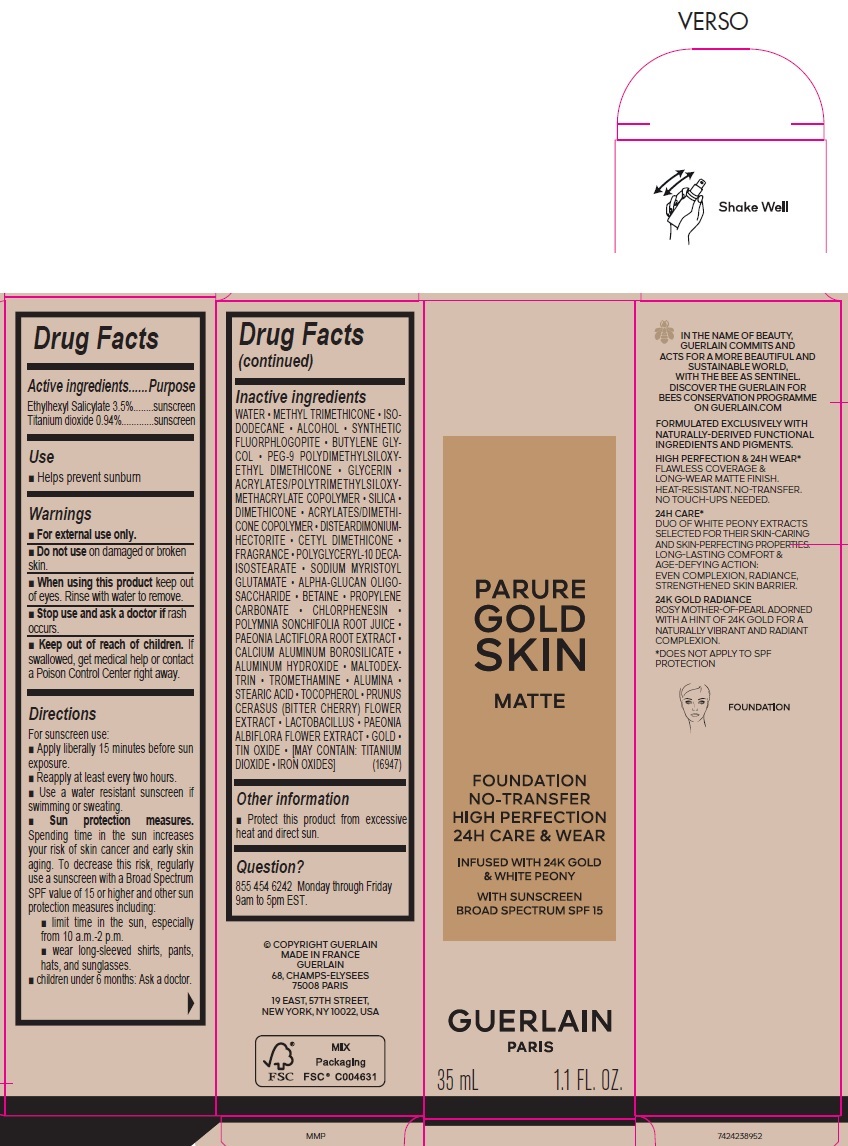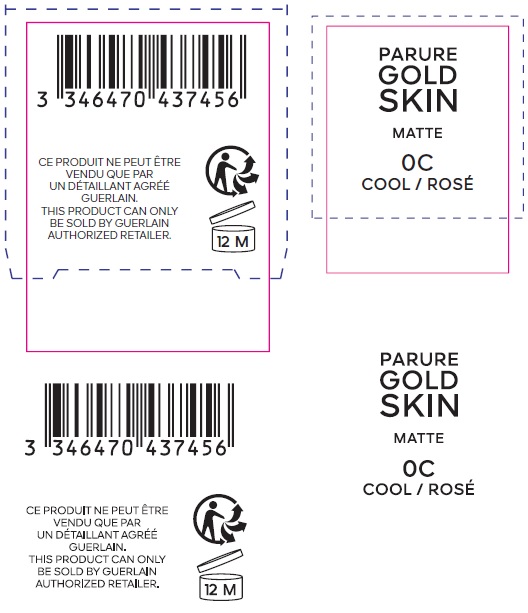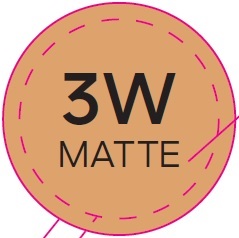 DRUG LABEL: PARURE GOLD SKIN MATTE FOUNDATION NO-TRANSFER HIGH PERFECTION 24H CARE AND WEAR INFUSED WITH 24K GOLD AND WHITE PEONY WITH SUNSCREEN BROADSPECTRUM SPF 15 0C
NDC: 49817-2080 | Form: EMULSION
Manufacturer: Guerlain
Category: otc | Type: HUMAN OTC DRUG LABEL
Date: 20231108

ACTIVE INGREDIENTS: OCTISALATE 35 mg/1 mL; TITANIUM DIOXIDE 9.4 mg/1 mL
INACTIVE INGREDIENTS: WATER; METHYL TRIMETHICONE; ISODODECANE; ALCOHOL; MAGNESIUM POTASSIUM ALUMINOSILICATE FLUORIDE; BUTYLENE GLYCOL; PEG-9 POLYDIMETHYLSILOXYETHYL DIMETHICONE; GLYCERIN; SILICON DIOXIDE; DIMETHICONE; DISTEARDIMONIUM HECTORITE; SODIUM MYRISTOYL GLUTAMATE; .ALPHA.-GLUCAN OLIGOSACCHARIDE; BETAINE; PROPYLENE CARBONATE; CHLORPHENESIN; SMALLANTHUS SONCHIFOLIUS ROOT JUICE; PAEONIA LACTIFLORA ROOT; CALCIUM ALUMINUM BOROSILICATE; ALUMINUM HYDROXIDE; MALTODEXTRIN; TROMETHAMINE; ALUMINUM OXIDE; STEARIC ACID; TOCOPHEROL; PRUNUS CERASUS FLOWER; PAEONIA LACTIFLORA FLOWER; GOLD; STANNIC OXIDE

PARURE GOLD SKIN MATTE FOUNDATION NO-TRANSFER HIGH PERFECTION 24H CARE & WEAR INFUSED WITH 24K GOLD & WHITE PEONY WITH SUNSCREEN BROADSPECTRUM SPF 15 0C

Active ingredients

Ethylhexyl Salicylate 3.5%

Titanium dioxide 0.94%

Purpose

sunscreen

Use

- Helps prevent sunburn

Warnings

- For external use only.

Do not use

- on damaged or broken skin.

When using this product

- keep out of eyes. Rinse with water to remove.

Stop use and ask a doctor if

- rash occurs.

Keep out of reach of children.

- If swallowed, get medical help or contact a Poison Control Center right away.

Directions

For sunscreen use:

- Apply liberally 15 minutes before sun exposure.
- Reapply at least every two hours.
- Use a water resistant sunscreen if swimming or sweating.
- Spending time in the sun increases your risk of skin cancer and early skin aging. To decrease this risk, regularly use a sunscreen with a Broad Spectrum SPF value of 15 or higher and other sun protection measures including: Sun protection measures.
- limit time in the sun, especially from 10 a.m.-2 p.m.
- wear long-sleeved shirts, pants, hats, and sunglasses.
- children under 6 months: Ask a doctor.

Inactive ingredients

WATER • METHYL TRIMETHICONE • ISODODECANE • ALCOHOL • SYNTHETIC FLUORPHLOGOPITE • BUTYLENE GLYCOL • PEG-9 POLYDIMETHYLSILOXYETHYL DIMETHICONE • GLYCERIN • ACRYLATES/POLYTRIMETHYLSILOXYMETHACRYLATE COPOLYMER • SILICA • DIMETHICONE • ACRYLATES/DIMETHICONE COPOLYMER • DISTEARDIMONIUMHECTORITE • CETYL DIMETHICONE • FRAGRANCE • POLYGLYCERYL-10 DECAISOSTEARATE • SODIUM MYRISTOYL GLUTAMATE • ALPHA-GLUCAN OLIGOSACCHARIDE • BETAINE • PROPYLENE CARBONATE • CHLORPHENESIN • POLYMNIA SONCHIFOLIA ROOT JUICE • PAEONIA LACTIFLORA ROOT EXTRACT • CALCIUM ALUMINUM BOROSILICATE • ALUMINUM HYDROXIDE • MALTODEXTRIN • TROMETHAMINE • ALUMINA • STEARIC ACID • TOCOPHEROL • PRUNUS CERASUS (BITTER CHERRY) FLOWER EXTRACT • LACTOBACILLUS • PAEONIA ALBIFLORA FLOWER EXTRACT • GOLD • TIN OXIDE • [MAY CONTAIN: TITANIUM DIOXIDE • IRON OXIDES] (16947)

Other information

- Protect this product from excessive heat and direct sun.

Question?

855 454 6242 Monday through Friday 9am to 5pm EST.